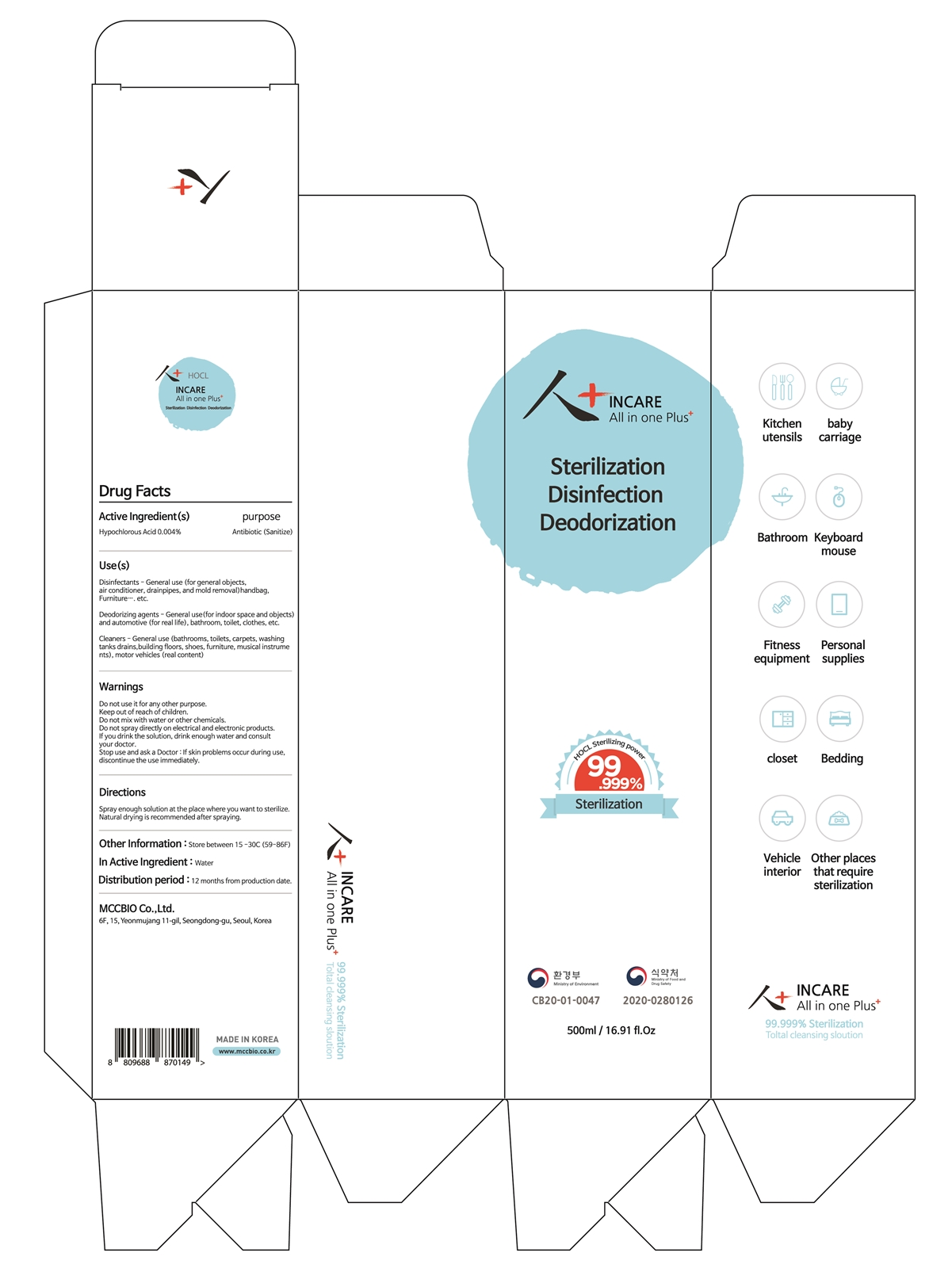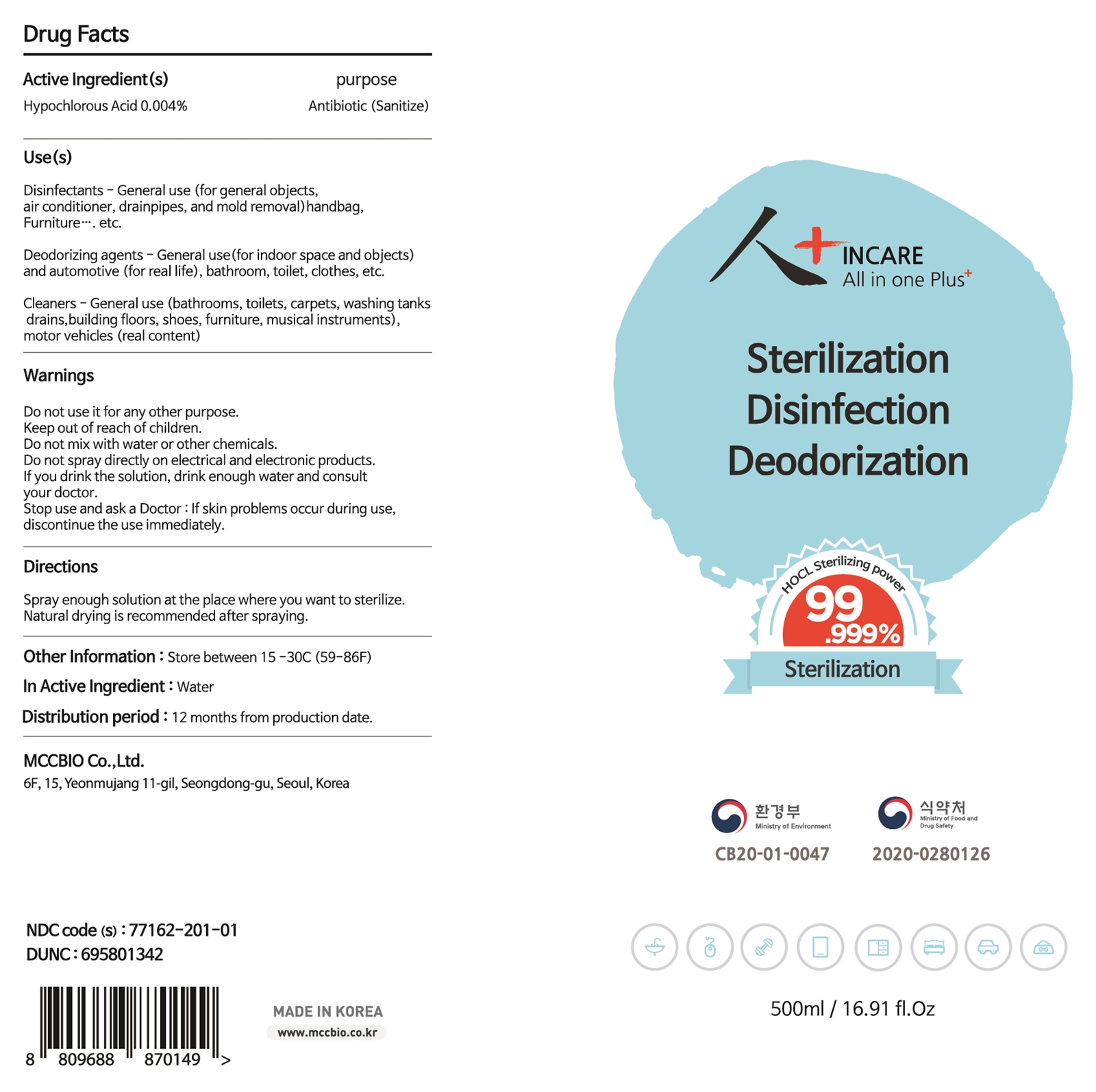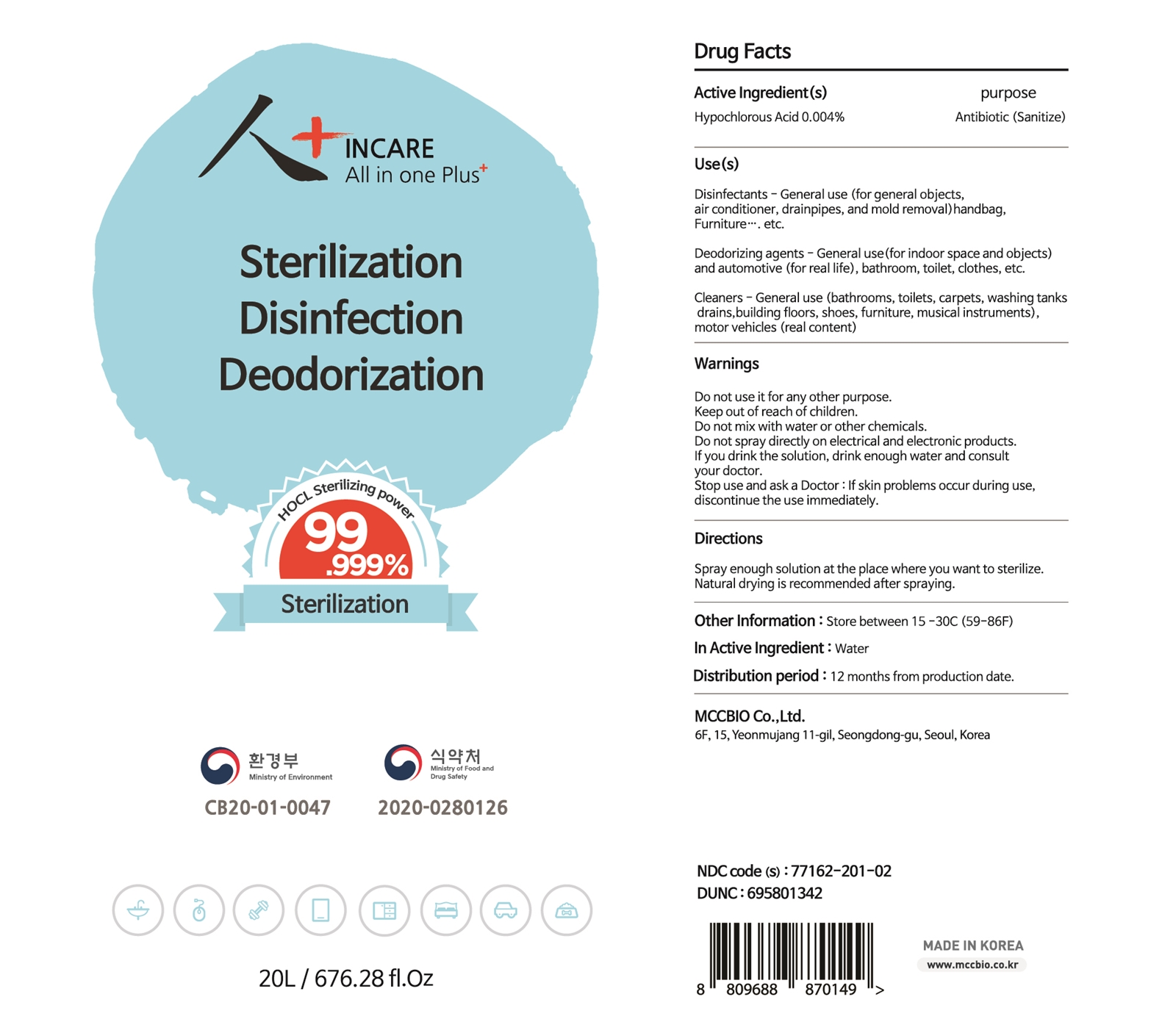 DRUG LABEL: INCARE All in one Plus
NDC: 77162-201 | Form: LIQUID
Manufacturer: MCCBIO CO., LTD
Category: otc | Type: HUMAN OTC DRUG LABEL
Date: 20220111

ACTIVE INGREDIENTS: HYPOCHLOROUS ACID 0.004 g/100 mL
INACTIVE INGREDIENTS: WATER 99.996 mL/100 mL

77162-201

Active Ingredient(s)

Hypochlorous Acid 0.004%

Purpose

Antibiotic (Sanitize)

Use(s)

Disinfectants - General use (for general objects, air conditioner, drainpipes, and mold removal) handbag, Furniture, etc.

Deodorizing agents - General use (for indoor space and objects) and automotive (for real life), bathroom, toilet, clothes, etc.

Cleaners - General use (bathrooms, toilets, carpets, washing tanks drains, building floors, shoes, furniture, musical instruments), motor vehicles (real content)

Warnings

Do not use it for any other purpose.

Warnings

Do not mix with water or other chemicals.

Do not spary directly on electrical and electronic products.

Warnings

Keep out of reach of children.

Warnings

If you drink the solution, drink enough water and consult your doctor.

Stop use and ask a Doctor: If skin problems occur during use, discontinue the use immediately.

Directions

Spray enough solution at the place where you want to sterilize.

Natural drying is recommended after spraying.

Other Information

Store between 15-30C (59-86F)

Inactive Ingredient

Water